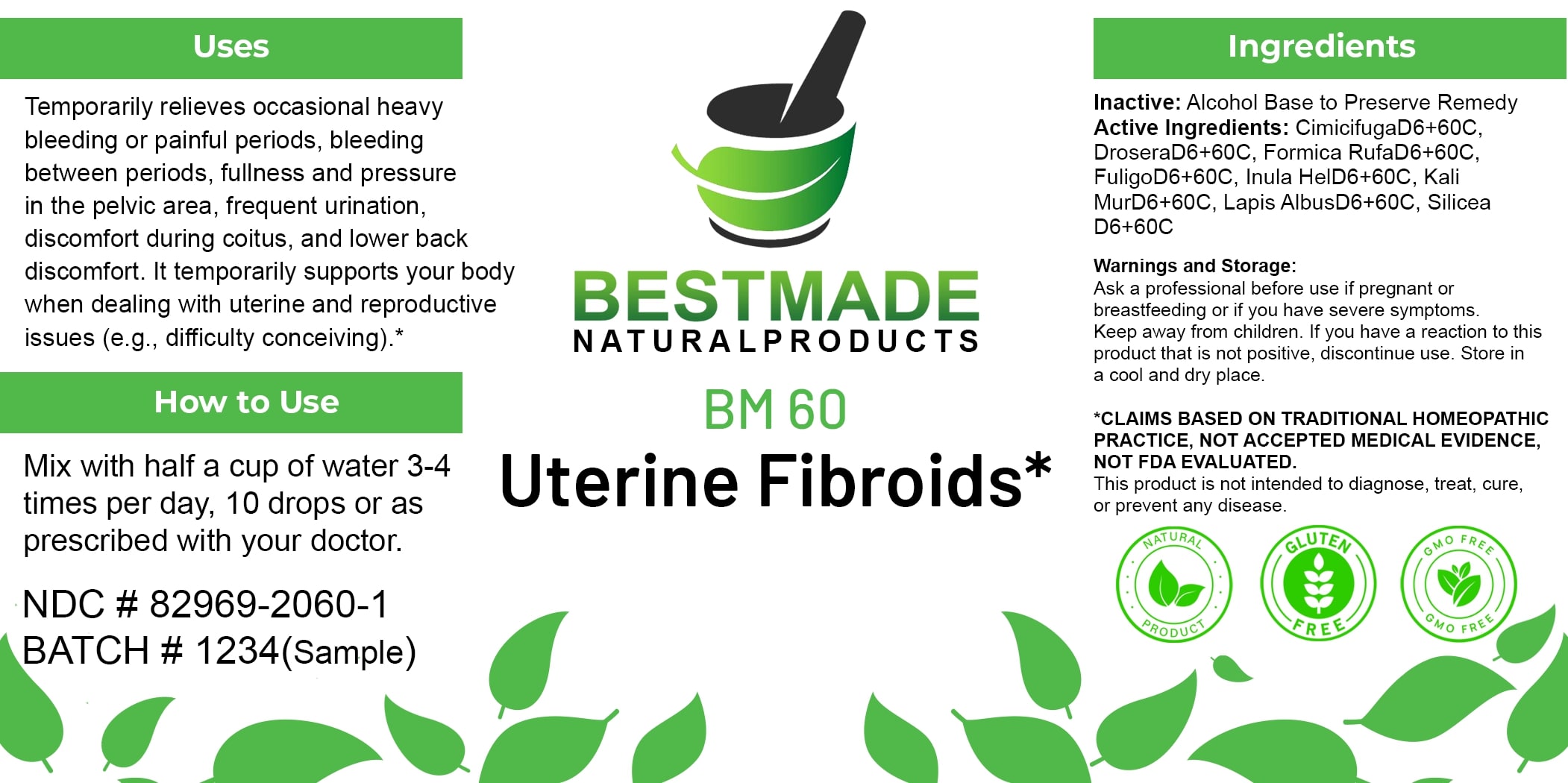 DRUG LABEL: Bestmade Natural Products BM60
NDC: 82969-2060 | Form: LIQUID
Manufacturer: Bestmade Natural Products
Category: homeopathic | Type: HUMAN OTC DRUG LABEL
Date: 20250325

ACTIVE INGREDIENTS: FORMICA RUFA 30 [hp_C]/30 [hp_C]; INULA HELENIUM ROOT 30 [hp_C]/30 [hp_C]; POTASSIUM CHLORIDE 30 [hp_C]/30 [hp_C]; DROSERA ROTUNDIFOLIA WHOLE 30 [hp_C]/30 [hp_C]; SILICA 30 [hp_C]/30 [hp_C]; CALCIUM HEXAFLUOROSILICATE 30 [hp_C]/30 [hp_C]; FULIGO SEPTICA 30 [hp_C]/30 [hp_C]; ACTAEA CIMICIFUGA WHOLE 30 [hp_C]/30 [hp_C]
INACTIVE INGREDIENTS: ALCOHOL 30 [hp_C]/30 [hp_C]

Uterine Fibroids Natural Remedy (BM60) 30ml

DOSAGE AND ADMINISTRATION

How to Use

Mix with half a cup of water 3-4 times per day, 10 drops or as prescribed with your doctor.

Uses

Temporarily relieves occasional heavy bleeding or painful periods, bleeding between periods, fullness and pressure in the pelvic area, frequent urination, discomfort during coitus, and lower back discomfort. It temporarily supports your body when dealing with uterine and reproductive issues (e.g., difficulty conceiving).*

*CLAIMS BASED ON TRADITIONAL HOMEOPATHIC PRACTICE, NOT ACCEPTED MEDICAL EVIDENCE, NOT FDA EVALUATED. This product is not intended to diagnose, treat, cure, or prevent any disease.

INACTIVE INGREDIENT

Ingredients

Inactive: Alcohol Base to Preserve Remedy

ACTIVE INGREDIENT

Active Ingredients: CimicifugaD6+60C, DroseraD6+60C, Formica RufaD6+60C, FuligoD6+60C, Inula HelD6+60C, Kali MurD6+60C, Lapis AlbusD6+60C, Silicea D6+60C

KEEP OUT OF REACH OF CHILDREN

Warnings and Storage:

Ask a professional before use if pregnant or breastfeeding or if you have severe symptoms. Keep away from children. If you have a reaction to this product that is not positive, discontinue use. Store in a cool and dry place.

Uses

Temporarily relieves occasional heavy bleeding or painful periods, bleeding between periods, fullness and pressure in the pelvic area, frequent urination, discomfort during coitus, and lower back discomfort. It temporarily supports your body when dealing with uterine and reproductive issues (e.g., difficulty conceiving).*

*CLAIMS BASED ON TRADITIONAL HOMEOPATHIC PRACTICE, NOT ACCEPTED MEDICAL EVIDENCE, NOT FDA EVALUATED. This product is not intended to diagnose, treat, cure, or prevent any disease.

Warnings and Storage:

Ask a professional before use if pregnant or breastfeeding or if you have severe symptoms. Keep away from children. If you have a reaction to this product that is not positive, discontinue use. Store in a cool and dry place.

*CLAIMS BASED ON TRADITIONAL HOMEOPATHIC PRACTICE, NOT ACCEPTED MEDICAL EVIDENCE, NOT FDA EVALUATED. This product is not intended to diagnose, treat, cure, or prevent any disease.

Entire package label